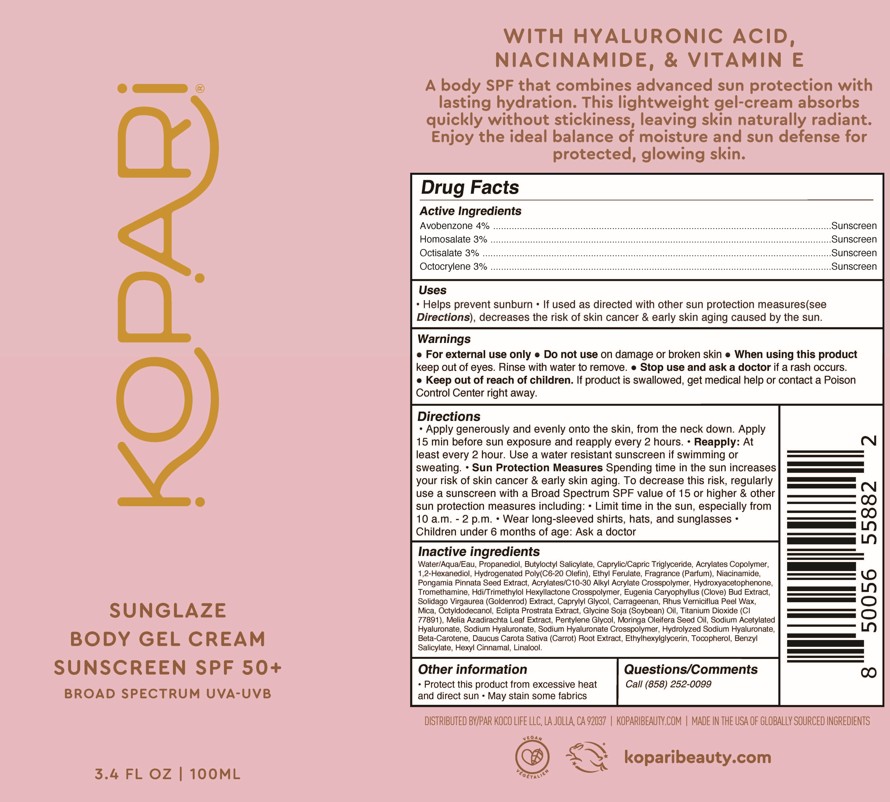 DRUG LABEL: Sunglaze Body Gel Cream Sunscreen SPF50
NDC: 84130-017 | Form: CREAM
Manufacturer: Koco Life LLC
Category: otc | Type: HUMAN OTC DRUG LABEL
Date: 20250909

ACTIVE INGREDIENTS: OCTISALATE 30 mg/1 mL; AVOBENZONE 40 mg/1 mL; HOMOSALATE 30 mg/1 mL; OCTOCRYLENE 30 mg/1 mL
INACTIVE INGREDIENTS: BETA-CAROTENE; ETHYL FERULATE; PONGAMIA PINNATA SEED; CLOVE; BENZYL SALICYLATE; CAPRYLYL GLYCOL; ECLIPTA PROSTRATA LEAF; MELIA AZADIRACHTA LEAF; NIACINAMIDE; SODIUM ACETYLATED HYALURONATE; SOLIDAGO VIRGAUREA WHOLE; CAPRYLIC/CAPRIC TRIGLYCERIDE; CARROT; HDI/TRIMETHYLOL HEXYLLACTONE CROSSPOLYMER; HYDROGENATED POLY(C6-20 OLEFIN); GLYCINE SOJA (SOYBEAN) OIL UNSAPONIFIABLES; HEXYL CINNAMAL; MICA; MORINGA OLEIFERA SEED OIL; OCTYLDODECANOL; BUTYLOCTYL SALICYLATE; CARRAGEENAN; RHUS VERNICIFLUA PEEL WAX; PEG-9 DIGLYCIDYL ETHER/SODIUM HYALURONATE CROSSPOLYMER; WATER; PROPANEDIOL; ACRYLATES/C10-30 ALKYL ACRYLATE CROSSPOLYMER (60000 MPA.S); LINALOOL; PENTYLENE GLYCOL; TITANIUM DIOXIDE; TOCOPHEROL; TROMETHAMINE; 1,2-HEXANEDIOL; ETHYLHEXYLGLYCERIN; SODIUM HYALURONATE; HYDROXYACETOPHENONE

Sunglaze Body Gel Cream Sunscreen SPF50+

Active ingredients

Avobenzone 4%

Homosalate 3%

Octisalate 3%

Octocrylene 3%

Purpose

Avobenzone 4%..................................Sunscreen

Homosalate 3%..................................Sunscreen

Octisalate 3%..................................Sunscreen

Octocrylene 3%..................................Sunscreen

Uses

• Helps prevent sunburn • If used as directed with other sun protection measures(see Directions), decreases the risk of skin cancer & early skin aging caused by the sun.

Warnings

- For external use only

- When using this product keep out of eyes. Rinse with water to remove

- Stop use and ask a doctor if a rash occurs.

- Keep out of reach of children. If product is swallowed, get medical help or contact a Poison Control Center right away.

Directions

• Apply generously and evenly onto the skin, from the neck down. Apply 15 min before sun exposure and reapply every 2 hours. • Reapply: At least every 2 hour. Use a water resistant sunscreen if swimming or sweating. • Sun Protection Measures Spending time in the sun increases your risk of skin cancer & early skin aging. To decrease this risk, regularly use a sunscreen with a Broad Spectrum SPF value of 15 or higher & other sun protection measures including: • Limit time in the sun, especially from 10 a.m. - 2 p.m. • Wear long-sleeved shirts, hats, and sunglasses • Children under 6 months of age: Ask a doctor

Inactive ingredients

Water/Aqua/Eau, Propanediol, Butyloctyl Salicylate, Caprylic/Capric Triglyceride, Acrylates Copolymer, 1,2-Hexanediol, Hydrogenated Poly(C6-20 Olefin), Ethyl Ferulate, Fragrance (Parfum), Niacinamide, Pongamia Pinnata Seed Extract, Acrylates/C10-30 Alkyl Acrylate Crosspolymer, Hydroxyacetophenone, Tromethamine, Hdi/Trimethylol Hexyllactone Crosspolymer, Eugenia Caryophyllus (Clove) Bud Extract, Solidago Virgaurea (Goldenrod) Extract, Caprylyl Glycol, Carrageenan, Rhus Verniciflua Peel Wax, Mica, Octyldodecanol, Eclipta Prostrata Extract, Glycine Soja (Soybean) Oil, Titanium Dioxide (CI 77891), Melia Azadirachta Leaf Extract, Pentylene Glycol, Moringa Oleifera Seed Oil, Sodium Acetylated Hyaluronate, Sodium Hyaluronate, Sodium Hyaluronate Crosspolymer, Hydrolyzed Sodium Hyaluronate, Beta-Carotene, Daucus Carota Sativa (Carrot) Root Extract, Ethylhexylglycerin, Tocopherol, Benzyl Salicylate, Hexyl Cinnamal, Linalool

Other information

Protect this product from excessive heatand direct sun • May stain some fabrics

Questions/Comments?

Call (858) 252-0099

PACKAGE LABEL

Kopari

Sunglaze

Body Gel Cream

Sunscreen SPF 50+

Broad Spectrum UVA-UVB

3.4 Fl Oz | 100ML